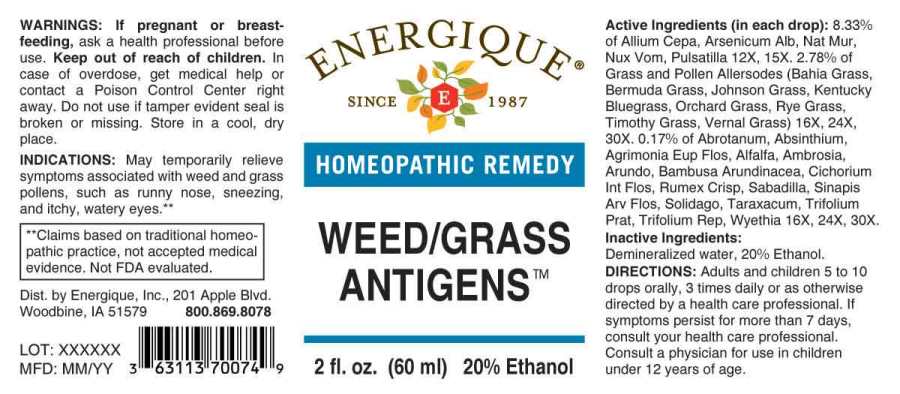 DRUG LABEL: Weed Grass Antigens
NDC: 44911-0553 | Form: LIQUID
Manufacturer: Energique, Inc.
Category: homeopathic | Type: HUMAN OTC DRUG LABEL
Date: 20241031

ACTIVE INGREDIENTS: ONION 12 [hp_X]/1 mL; ARSENIC TRIOXIDE 12 [hp_X]/1 mL; SODIUM CHLORIDE 12 [hp_X]/1 mL; STRYCHNOS NUX-VOMICA SEED 12 [hp_X]/1 mL; PULSATILLA PRATENSIS WHOLE 12 [hp_X]/1 mL; ARTEMISIA ABROTANUM FLOWERING TOP 16 [hp_X]/1 mL; WORMWOOD 16 [hp_X]/1 mL; AGRIMONIA EUPATORIA FLOWER 16 [hp_X]/1 mL; MEDICAGO SATIVA WHOLE 16 [hp_X]/1 mL; AMBROSIA ARTEMISIIFOLIA WHOLE 16 [hp_X]/1 mL; ARUNDO PLINIANA ROOT 16 [hp_X]/1 mL; BAMBUSA BAMBOS LEAF 16 [hp_X]/1 mL; CICHORIUM INTYBUS FLOWER 16 [hp_X]/1 mL; POA PRATENSIS POLLEN 16 [hp_X]/1 mL; DACTYLIS GLOMERATA TOP 16 [hp_X]/1 mL; CYNODON DACTYLON POLLEN 16 [hp_X]/1 mL; SORGHUM HALEPENSE POLLEN 16 [hp_X]/1 mL; LOLIUM PERENNE POLLEN 16 [hp_X]/1 mL; ANTHOXANTHUM ODORATUM POLLEN 16 [hp_X]/1 mL; PASPALUM NOTATUM POLLEN 16 [hp_X]/1 mL; PHLEUM PRATENSE TOP 16 [hp_X]/1 mL; RUMEX CRISPUS ROOT 16 [hp_X]/1 mL; SCHOENOCAULON OFFICINALE SEED 16 [hp_X]/1 mL; SINAPIS ARVENSIS FLOWERING/FRUITING TOP 16 [hp_X]/1 mL; SOLIDAGO VIRGAUREA FLOWERING TOP 16 [hp_X]/1 mL; TARAXACUM OFFICINALE 16 [hp_X]/1 mL; TRIFOLIUM PRATENSE FLOWER 16 [hp_X]/1 mL; TRIFOLIUM REPENS FLOWER 16 [hp_X]/1 mL; WYETHIA HELENIOIDES ROOT 16 [hp_X]/1 mL
INACTIVE INGREDIENTS: WATER; ALCOHOL

DRUG FACTS:

ACTIVE INGREDIENTS:

(in each drop): 8.33% of Allium Cepa 12X, 15X, Arsenicum Album 12X, 15X, Natrum Muriaticum 12X, 15X, Nux Vomica 12X, 15X, Pulsatilla (Pratensis) 12X, 15X. 2.78% of Kentucky Bluegrass 16X, 24X, 30X, Orchard Grass 16X, 24X, 30X, Bermuda Grass 16X, 24X, 30X, Johnson Grass 16X, 24X, 30X, Rye Grass 16X, 24X, 30X , Vernal Grass 16X, 24X, 30X, Bahia Grass 16X, 24X, 30X, Timothy Grass 16X, 24X, 30X. 0.17% of Abrotanum (Artemisia Abrotanum) 16X, 24X, 30X, Absinthium 16X, 24X, 30X, Agrimonia Eupatoria, Flos, 16X, 24X, 30X, Alfalfa 16X, 24X, 30X, Ambrosia Artemisiaefolia 16X, 24X, 30X, Arundo Mauritanica 16X, 24X, 30X, Bambusa Arundinacea 16X, 24X, 30X, Cichorium Intybus, Flos, 16X, 24X, 30X, Rumex Crispus, 16X, 24, 30X, Sabadilla 16X, 24X, 30X, Sinapis Arvensis, Flos, 16X, 24X, 30X, Solidago Virgaurea 16X, 24X, 30X, Taraxacum Officinale 16X, 24X, 30X, Trifolium Pratense 16X, 24X, 30X, Trifolium Repens 16X, 24X, 30X, Wyethia Helenioides 16X, 24X, 30X.

INDICATIONS:

May temporarily relieve symptoms associated with weed and grass pollens such as unny nose, sneezing, and itchy, watery eyes.**

**Claims based on traditional homeopathic practice, not accepted medical evidence. Not FDA evaluated.

WARNINGS:

If pregnant or breast-feeding, ask a health professional before use.

Keep out of reach of children. In case of overdose, get medical help or contact a Poison Control Center right away.

Do not use if tamper evident seal is broken or missing.

Store in a cool, dry place.

Keep out of reach of children. In case of overdose, get medical help or contact a Poison Control Center right away.

DIRECTIONS:

Adults and children 5 to 10 drops orally, 3 times daily or as otherwise directed by a health care professional. If symptoms persist for more than 7 days, consult your health care professional. Consult a physician for use in children under 12 years of age.

INDICATIONS:

May temporarily relieve symptoms associated with weed and grass pollens such as unny nose, sneezing, and itchy, watery eyes.**

**Claims based on traditional homeopathic practice, not accepted medical evidence. Not FDA evaluated.

INACTIVE INGREDIENTS:

Demineralized water, 20% Ethanol.

QUESTIONS:

Dist. by

Energique, Inc.

201 Apple Blvd.

Woodbine, IA 51579 800.869.8078

PACKAGE LABEL DISPLAY:

ENERGIQUE

SINCE 1987

HOMEOPATHIC REMEDY

WEED/GRASS ANTIGENS

2 fl. oz. (60 ml)